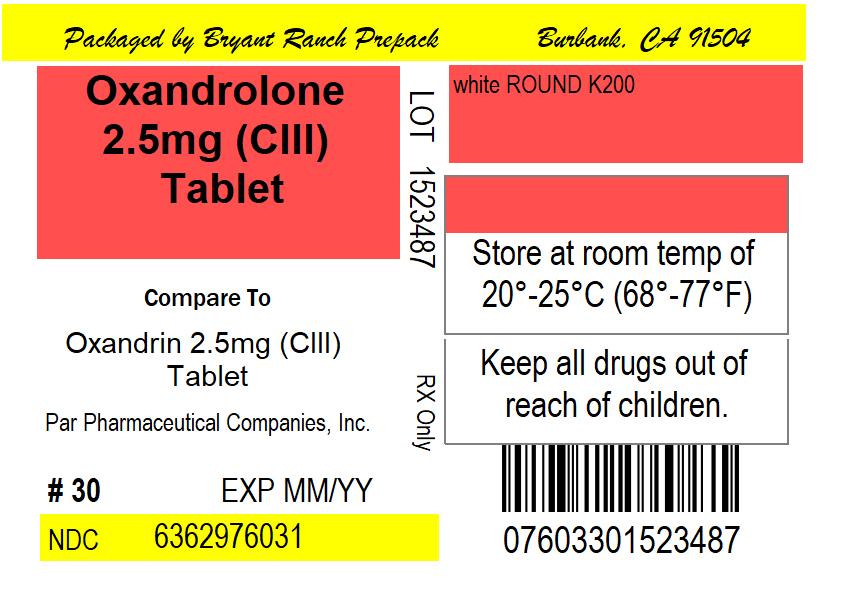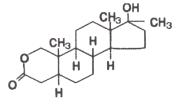 DRUG LABEL: Oxandrolone
NDC: 63629-7603 | Form: TABLET
Manufacturer: Bryant Ranch Prepack
Category: prescription | Type: HUMAN PRESCRIPTION DRUG LABEL
Date: 20220429
DEA Schedule: CIII

ACTIVE INGREDIENTS: OXANDROLONE 2.5 mg/1 1
INACTIVE INGREDIENTS: LACTOSE MONOHYDRATE; STARCH, CORN; MAGNESIUM STEARATE

Oxandrolone Tablet, USP

BOXED WARNINGS

PELIOSIS HEPATIS, A CONDITION IN WHICH LIVER AND SOMETIMES SPLENIC TISSUE IS REPLACED WITH BLOOD-FILLED CYSTS, HAS BEEN REPORTED IN PATIENTS RECEIVING ANDROGENIC ANABOLIC STEROID THERAPY. THESE CYSTS ARE SOMETIMES PRESENT WITH MINIMAL HEPATIC DYSFUNCTION, BUT AT OTHER TIMES THEY HAVE BEEN ASSOCIATED WITH LIVER FAILURE. THEY ARE OFTEN NOT RECOGNIZED UNTIL LIFE-THREATENING LIVER FAILURE OR INTRA-ABDOMINAL HEMORRHAGE DEVELOPS. WITHDRAWAL OF DRUG USUALLY RESULTS IN COMPLETE DISAPPEARANCE OF LESIONS. LIVER CELL TUMORS ARE ALSO REPORTED. MOST OFTEN THESE TUMORS ARE BENIGN AND ANDROGEN-DEPENDENT, BUT FATAL MALIGNANT TUMORS HAVE BEEN REPORTED. WITHDRAWAL OF DRUG OFTEN RESULTS IN REGRESSION OR CESSATION OF PROGRESSION OF THE TUMOR. HOWEVER, HEPATIC TUMORS ASSOCIATED WITH ANDROGENS OR ANABOLIC STEROIDS ARE MUCH MORE VASCULAR THAN OTHER HEPATIC TUMORS AND MAY BE SILENT UNTIL LIFE-THREATENING INTRA-ABDOMINAL HEMORRHAGE DEVELOPS. BLOOD LIPID CHANGES THAT ARE KNOWN TO BE ASSOCIATED WITH INCREASED RISK OF ATHEROSCLEROSIS ARE SEEN IN PATIENTS TREATED WITH ANDROGENS OR ANABOLIC STEROIDS. THESE CHANGES INCLUDE DECREASED HIGH-DENSITY LIPOPROTEINS AND SOMETIMES INCREASED LOW-DENSITY LIPOPROTEINS. THE CHANGES MAY BE VERY MARKED AND COULD HAVE A SERIOUS IMPACT ON THE RISK OF ATHEROSCLEROSIS AND CORONARY ARTERY DISEASE.

DESCRIPTION

Oxandrolone oral tablets contain 2.5 mg or 10 mg of the anabolic steroid oxandrolone. Oxandrolone is 17β-hydroxy-17α-methyl-2-oxa-5α-androstan-3-one with the following structural formula:

Molecular Formula: C19H30O3

Molecular Weight: 306.44

Inactive ingredients include: corn starch, lactose monohydrate, magnesium stearate, and hypromellose.

Meets USP Dissolution Test 2.

CLINICAL PHARMACOLOGY

Anabolic steroids are synthetic derivatives of testosterone. Certain clinical effects and adverse reactions demonstrate the androgenic properties of this class of drugs. Complete dissociation of anabolic and androgenic effects has not been achieved. The actions of anabolic steroids are therefore similar to those of male sex hormones with the possibility of causing serious disturbances of growth and sexual development if given to young children. Anabolic steroids suppress the gonadotropic functions of the pituitary and may exert a direct effect upon the testes.

During exogenous administration of anabolic androgens, endogenous testosterone release is inhibited through inhibition of pituitary luteinizing hormone (LH). At large doses, spermatogenesis may be suppressed through feedback inhibition of pituitary follicle-stimulating hormone (FSH).

Anabolic steroids have been reported to increase low-density lipoproteins and decrease high-density lipoproteins. These levels revert to normal on discontinuation of treatment.

INDICATIONS AND USAGE

Oxandrolone is indicated as adjunctive therapy to offset the protein catabolism associated with prolonged administration of corticosteroids, and for the relief of the bone pain frequently accompanying osteoporosis (see DOSAGE AND ADMINISTRATION).

DRUG ABUSE AND DEPENDENCE

Oxandrolone is classified as a controlled substance under the Anabolic Steroids Control Act of 1990 and has been assigned to Schedule III (non-narcotic).

CONTRAINDICATIONS

1. Known or suspected carcinoma of the prostate or the male breast.
2. Carcinoma of the breast in females with hypercalcemia (androgenic anabolic steroids may stimulate osteolytic bone resorption).
3. Pregnancy, because of possible masculinization of the fetus. Oxandrolone has been shown to cause embryotoxicity, fetotoxicity, infertility, and masculinization of female animal offspring when given in doses 9 times the human dose.
4. Nephrosis, the nephrotic phase of nephritis.
5. Hypercalcemia.

WARNINGS

Cholestatic hepatitis and jaundice may occur with 17-alpha-alkylated androgens at a relatively low dose. If cholestatic hepatitis with jaundice appears or if liver function tests become abnormal, oxandrolone should be discontinued and the etiology should be determined. Drug-induced jaundice is reversible when the medication is discontinued.

In patients with breast cancer, anabolic steroid therapy may cause hypercalcemia by stimulating osteolysis. Oxandrolone therapy should be discontinued if hypercalcemia occurs.

Edema with or without congestive heart failure may be a serious complication in patients with pre-existing cardiac, renal, or hepatic disease. Concomitant administration of adrenal cortical steroid or ACTH may increase the edema.

In children, androgen therapy may accelerate bone maturation without producing compensatory gain in linear growth. This adverse effect results in compromised adult height. The younger the child, the greater the risk of compromising final mature height. The effect on bone maturation should be monitored by assessing bone age of the left wrist and hand every 6 months (see PRECAUTIONS, Laboratory Tests).

Geriatric patients treated with androgenic anabolic steroids may be at an increased risk for the development of prostatic hypertrophy and prostatic carcinoma. ANABOLIC STEROIDS HAVE NOT BEEN SHOWN TO ENHANCE ATHLETIC ABILITY.

PRECAUTIONS

Concurrent dosing of oxandrolone and warfarin may result in unexpectedly large increases in the International Normalized Ratio (INR) or prothrombin time (PT). When oxandrolone is prescribed to patients being treated with warfarin, doses of warfarin may need to be decreased significantly to maintain the desirable INR level and diminish the risk of potentially serious bleeding (see PRECAUTIONS, Drug Interactions).

General

Women should be observed for signs of virilization (deepening of the voice, hirsutism, acne, clitoromegaly). Discontinuation of drug therapy at the time of evidence of mild virilism is necessary to prevent irreversible virilization. Some virilizing changes in women are irreversible even after prompt discontinuance of therapy and are not prevented by concomitant use of estrogens. Menstrual irregularities may also occur.

Anabolic steroids may cause suppression of clotting factors II, V, VII, and X, and an increase in prothrombin time.

Information for Patients

The physician should instruct patients to report immediately any use of warfarin and any bleeding.

The physician should instruct patients to report any of the following side effects of androgens:

Males:

Too frequent or persistent erections of the penis, appearance or aggravation of acne.

Females:

Hoarseness, acne, changes in menstrual periods, or more facial hair.

All patients:

Nausea, vomiting, changes in skin color, or ankle swelling.

Geriatric Use:

Certain geriatric use information is protected by marketing exclusivity.

Laboratory Tests

Women with disseminated breast carcinoma should have frequent determination of urine and serum calcium levels during the course of therapy (see WARNINGS).

Because of the hepatotoxicity associated with the use of 17-alpha-alkylated androgens, liver function tests should be obtained periodically.

Periodic (every 6 months) x-ray examinations of bone age should be made during treatment of children to determine the rate of bone maturation and the effects of androgen therapy on the epiphyseal centers.

Androgenic anabolic steroids have been reported to increase low-density lipoproteins and decrease high-density lipoproteins. Therefore, caution is required when administering these agents to patients with a history of cardiovascular disease or who are at risk for cardiovascular disease. Serum determination of lipid levels should be performed periodically and therapy adjusted accordingly.

Hemoglobin and hematocrit should be checked periodically for polycythemia in patients who are receiving high doses of anabolic steroids.

Drug Interactions

Anticoagulants:

Anabolic steroids may increase sensitivity to oral anticoagulants. Dosage of the anticoagulant may have to be decreased in order to maintain desired prothrombin time. Patients receiving oral anticoagulant therapy require close monitoring, especially when anabolic steroids are started or stopped.

Warfarin:

A multidose study of oxandrolone, given as 5 or 10 mg BID in 15 healthy subjects concurrently treated with warfarin, resulted in a mean increase in S-warfarin half-life from 26 to 48 hours and AUC from 4.55 to 12.08 ng•hr/mL; similar increases in R-warfarin half-life and AUC were also detected. Microscopic hematuria (9/15) and gingival bleeding (1/15) were also observed. A 5.5-fold decrease in the mean warfarin dose from 6.13 mg/day to 1.13 mg/day (approximately 80-85% reduction of warfarin dose), was necessary to maintain a target INR of 1.5. When oxandrolone therapy is initiated in a patient already receiving treatment with warfarin, the INR or prothrombin time (PT) should be monitored closely and the dose of warfarin adjusted as necessary until a stable target INR or PT has been achieved.

Furthermore, in patients receiving both drugs, careful monitoring of the INR or PT, and adjustment of the warfarin dosage if indicated are recommended when the oxandrolone dose is changed or discontinued. Patients should be closely monitored for signs and symptoms of occult bleeding.

Oral Hypoglycemic Agents:

Oxandrolone may inhibit the metabolism of oral hypoglycemic agents.

Adrenal Steroids or ACTH:

In patients with edema, concomitant administration with adrenal cortical steroids or ACTH may increase the edema.

Drug/Laboratory Test Interactions

Anabolic steroids may decrease levels of thyroxine-binding globulin, resulting in decreased total T4 serum levels and increased resin uptake of T3 and T4. Free thyroid hormone levels remain unchanged. In addition, a decrease in PBI and radioactive iodine uptake may occur.

Carcinogenesis, Mutagenesis, Impairment of Fertility

Animal Data:

Oxandrolone has not been tested in laboratory animals for carcinogenic or mutagenic effects. In 2-year chronic oral rat studies, a dose-related reduction of spermatogenesis and decreased organ weights (testes, prostate, seminal vesicles, ovaries, uterus, adrenals, and pituitary) were shown.

Human Data:

Liver cell tumors have been reported in patients receiving long-term therapy with androgenic anabolic steroids in high doses (see WARNINGS). Withdrawal of the drugs did not lead to regression of the tumors in all cases.

Geriatric patients treated with androgenic anabolic steroids may be at an increased risk for the development of prostatic hypertrophy and prostatic carcinoma.

Pregnancy

Teratogenic effects-Pregnancy Category X (see CONTRAINDICATIONS).

Nursing Mothers

It is not known whether anabolic steroids are excreted in human milk. Because of the potential of serious adverse reactions in nursing infants from oxandrolone, a decision should be made whether to discontinue nursing or to discontinue the drug, taking into account the importance of the drug to the mother.

Pediatric Use

Anabolic agents may accelerate epiphyseal maturation more rapidly than linear growth in children and the effect may continue for 6 months after the drug has been stopped. Therefore, therapy should be monitored by x-ray studies at 6-month intervals in order to avoid the risk of compromising adult height. Androgenic anabolic steroid therapy should be used very cautiously in children and only by specialists who are aware of the effects on bone maturation (see WARNINGS).

ADVERSE REACTIONS

Patients with moderate to severe COPD or COPD patients who are unresponsive to bronchodilators should be monitored closely for COPD exacerbation and fluid retention.

The following adverse reactions have been associated with use of anabolic steroids:

Hepatic

Cholestatic jaundice with, rarely, hepatic necrosis and death. Hepatocellular neoplasms and peliosis hepatis with long-term therapy (see WARNINGS). Reversible changes in liver function tests also occur including increased bromsulfophthalein (BSP) retention, changes in alkaline phosphatase and increases in serum bilirubin, aspartate aminotransferase (AST, SGOT) and alanine aminotransferase (ALT, SGPT).

In Males

Prepubertal:

Phallic enlargement and increased frequency or persistence of erections.

Postpubertal:

Inhibition of testicular function, testicular atrophy and oligospermia, impotence, chronic priapism, epididymitis, and bladder irritability.

In Females

Clitoral enlargement, menstrual irregularities.

CNS

Habituation, excitation, insomnia, depression, and changes in libido.

Hematologic

Bleeding in patients on concomitant anticoagulant therapy.

Breast

Gynecomastia.

Larynx

Deepening of the voice in females.

Hair

Hirsutism and male pattern baldness in females.

Skin

Acne (especially in females and prepubertal males).

Skeletal

Premature closure of epiphyses in children (see PRECAUTIONS, Pediatric Use).

Fluid and Electrolytes

Edema, retention of serum electrolytes (sodium chloride, potassium, phosphate, calcium).

Metabolic/Endocrine

Decreased glucose tolerance (see PRECAUTIONS, Laboratory Tests), increased creatinine excretion, increased serum levels of creatinine phosphokinase (CPK). Masculinization of the fetus. Inhibition of gonadotropin secretion.

OVERDOSAGE

No symptoms or signs associated with overdosage have been reported. It is possible that sodium and water retention may occur.

The oral LD50 of oxandrolone in mice and dogs is greater than 5,000 mg/kg. No specific antidote is known, but gastric lavage may be used.

DOSAGE AND ADMINISTRATION

Therapy with anabolic steroids is adjunctive to and not a replacement for conventional therapy. The duration of therapy with oxandrolone will depend on the response of the patient and the possible appearance of adverse reactions. Therapy should be intermittent.

Adults

The response of individuals to anabolic steroids varies. The daily adult dosage is 2.5 mg to 20 mg given in 2 to 4 divided doses. The desired response may be achieved with as little as 2.5 mg or as much as 20 mg daily. A course of therapy of 2 to 4 weeks is usually adequate. This may be repeated intermittently as indicated.

Children

For children the total daily dosage of oxandrolone is <0.1 mg per kilogram body weight or <0.045 mg per pound of body weight. This may be repeated intermittently as indicated.

HOW SUPPLIED

NDC: 63629-7603-1: 30 Tablets in a BOTTLE

NDC: 63629-7603-2: 100 Tablets in a BOTTLE

NDC: 63629-7603-3: 90 Tablets in a BOTTLE

PACKAGE LABEL

Oxandrolone 2.5mg (CIII) Tablet